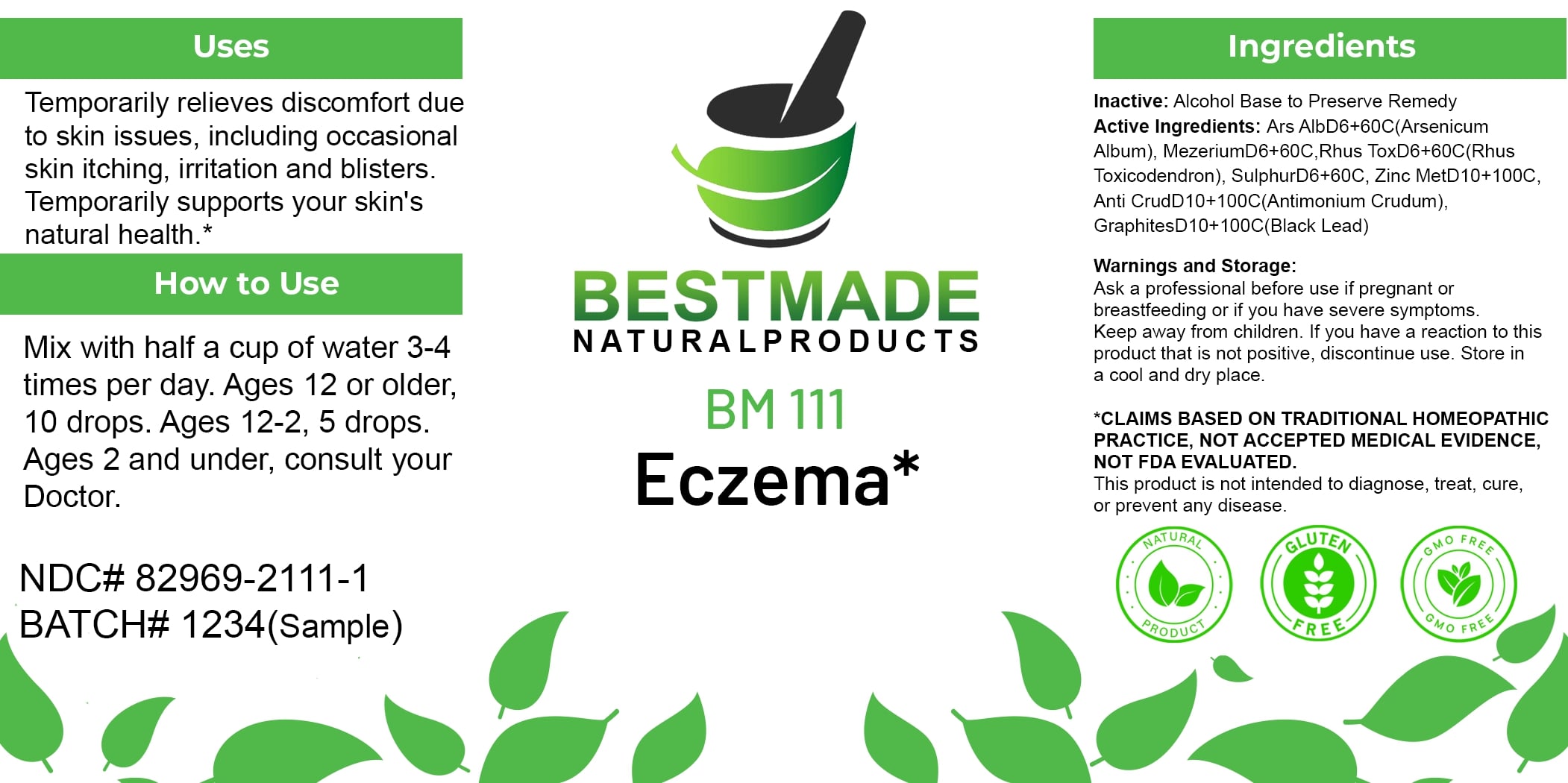 DRUG LABEL: Bestmade Natural Products BM111
NDC: 82969-2111 | Form: LIQUID
Manufacturer: Bestmade Natural Products
Category: homeopathic | Type: HUMAN OTC DRUG LABEL
Date: 20250207

ACTIVE INGREDIENTS: ZINC 30 [hp_C]/30 [hp_C]; GRAPHITE 30 [hp_C]/30 [hp_C]; DAPHNE MEZEREUM BARK 30 [hp_C]/30 [hp_C]; TOXICODENDRON PUBESCENS LEAF 30 [hp_C]/30 [hp_C]; ANTIMONY TRISULFIDE 30 [hp_C]/30 [hp_C]; SULFUR 30 [hp_C]/30 [hp_C]; ARSENIC TRIOXIDE 30 [hp_C]/30 [hp_C]
INACTIVE INGREDIENTS: ALCOHOL 30 [hp_C]/30 [hp_C]

BM111

DOSAGE AND ADMINISTRATION

How to Use

Mix with half a cup of water 3-4 times per day. Ages 12 or older, 10 drops. Ages 12-2, 5 drops. Ages 2 and under, consult your Doctor.

INACTIVE INGREDIENT

Ingredients

Inactive: Alcohol Base to Preserve Remedy

ACTIVE INGREDIENT

Active Ingredients: Ars AlbD6+60C(Arsenicum Album), MezereumD6+60C, Rhus ToxD6+60C(Rhus Toxicodendron), SulphurD6+60C, Zinc MetD10+100C, Anti CrudD10+100C(Antimonium Crudum), GraphitesD10+100C(Black Lead)

Uses

Temporarily relieves discomfort due to skin issues, including occasional skin itching, irritation and blisters. Temporarily supports your skin's natural health.*

*CLAIMS BASED ON TRADITIONAL HOMEOPATHIC PRACTICE, NOT ACCEPTED MEDICAL EVIDENCE. NOT FDA EVALUATED.

This product is not intended to diagnose, treat, cure, or prevent any disease.

Uses

Temporarily relieves discomfort due to skin issues, including occasional skin itching, irritation and blisters. Temporarily supports your skin's natural health.*

*CLAIMS BASED ON TRADITIONAL HOMEOPATHIC PRACTICE, NOT ACCEPTED MEDICAL EVIDENCE. NOT FDA EVALUATED.

This product is not intended to diagnose, treat, cure, or prevent any disease.

KEEP OUT OF REACH OF CHILDREN

Warnings and Storage:

Ask a professional before use if pregnant or breastfeeding or if you have severe symptoms. Keep away from children. If you have a reaction to this product that is not positive, discontinue use. Store in a cool and dry place.

Warnings and Storage:

Ask a professional before use if pregnant or breastfeeding or if you have severe symptoms. Keep away from children. If you have a reaction to this product that is not positive, discontinue use. Store in a cool and dry place.

*CLAIMS BASED ON TRADITIONAL HOMEOPATHIC PRACTICE, NOT ACCEPTED MEDICAL EVIDENCE. NOT FDA EVALUATED.

This product is not intended to diagnose, treat, cure, or prevent any disease.

Entire package label